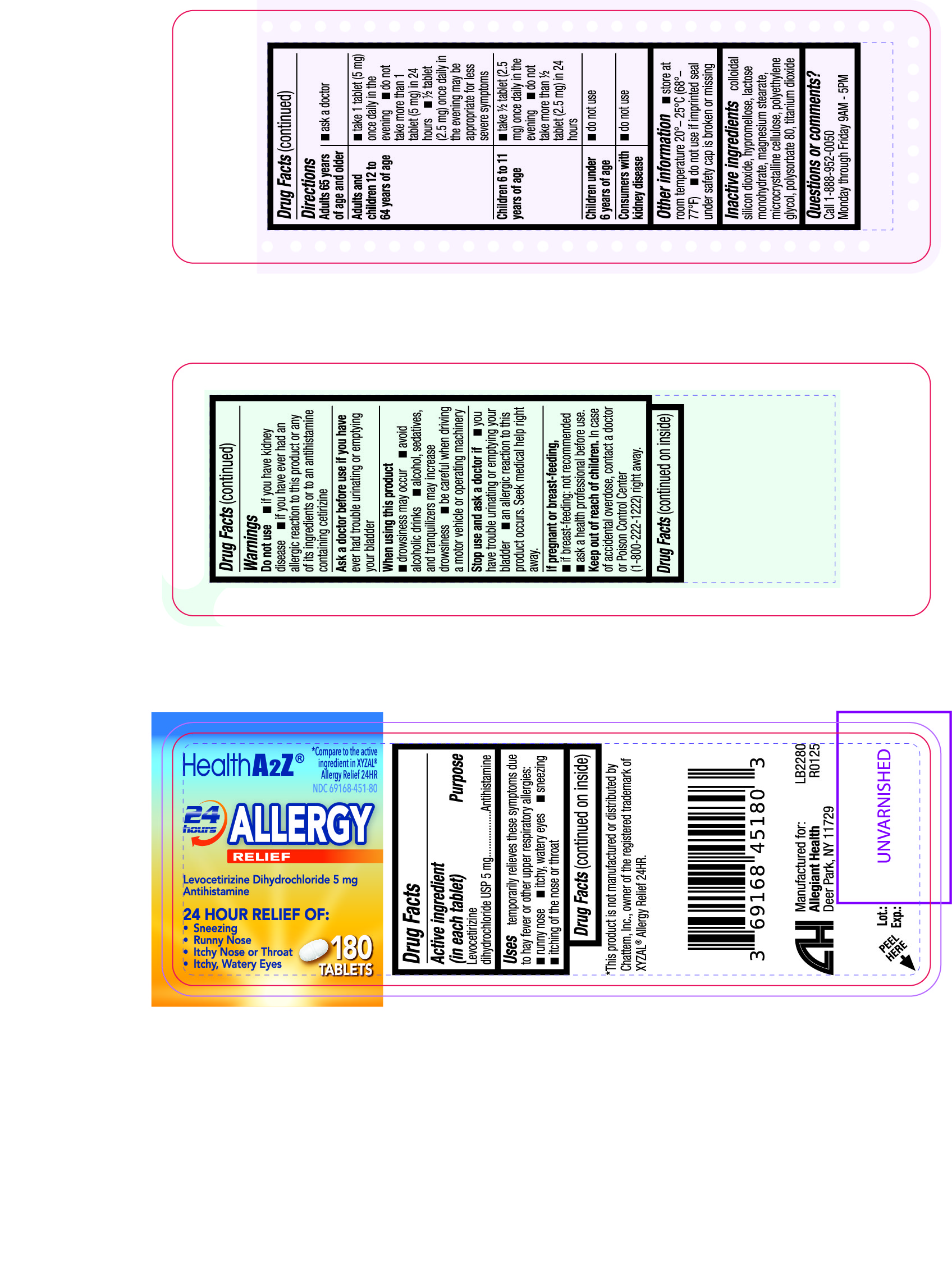 DRUG LABEL: Allery Relief 24HR
NDC: 69168-451 | Form: TABLET, FILM COATED
Manufacturer: Allegiant Health
Category: otc | Type: HUMAN OTC DRUG LABEL
Date: 20240402

ACTIVE INGREDIENTS: LEVOCETIRIZINE DIHYDROCHLORIDE 5 mg/1 1
INACTIVE INGREDIENTS: SILICON DIOXIDE; HYPROMELLOSE, UNSPECIFIED; LACTOSE MONOHYDRATE; MAGNESIUM STEARATE; MICROCRYSTALLINE CELLULOSE; POLYETHYLENE GLYCOL, UNSPECIFIED; POLYSORBATE 80; TITANIUM DIOXIDE

451 - Allergy Relief 24HR

Active ingredient(s)

Levocetirizine dihydrochloride USP 5 mg

Purpose

Antihistamine

Use(s)

temporarily relieves these symptoms due to hay fever or other respiratory allergies:
• runny nose
• sneezing
• itchy, watery eyes
• itching of the nose or throat

Warnings

Do not use

• if you have kidney disease
• if you have ever had an allergic reaction to this product or any of its ingredients or to an antihistamine containing cetirizine

Ask a doctor before use if

- ever had trouble urinating or emptying your bladder

When using this product

- drowsiness may occur
- avoid alcoholic drinks
- alcohol, sedatives, and tranquilizers may increase drowsiness
- be careful when driving a motor vehicle or operating machinery

Stop use and ask a doctor if

• you have trouble urinating or emptying your bladder
• an allergic reaction to this product occurs. Seek medical help right away.

If pregnant or breastfeeding,

- if breast-feeding: not recommended
- if pregnant: ask a health professional before use

Keep out of reach of children

In case of overdose, get medical help or contact a Poison Control Center right away (1-800-222-1222).

Directions

adults 65 years of age and older | - ask a doctor
adults and children 12 to 64 years of age | - take 1 tablet (5 mg) once daily in the evening - do not take more than 1 tablet (5 mg) in 24 hours - &frac12; tablet (2.5 mg) once daily in the evening may be appropriate for less severe symptoms
children 6 to 11 years of age | - take &frac12; tablet (2.5 mg) once daily in the evening - do not take more than &frac12; tablet (2.5 mg) in 24 hours
children under 6 years of age | - do not use
consumers with kidney disease | - do not use

Other information

- store at room temperature 20°– 25°C (68°– 77°F)
- do not use if imprinted seal under safety cap is broken or missing

Inactive ingredients

colloidal silicon dioxide, hypromellose, lactose monohydrate, magnesium stearate,
microcrystalline cellulose, polyethylene glycol, polysorbate 80, titanium dioxide

Questions/Comments

Call 1-888-952-0050 Monday through Friday 9AM - 5PM

Principal Display Panel

Allergy Relief 24HR